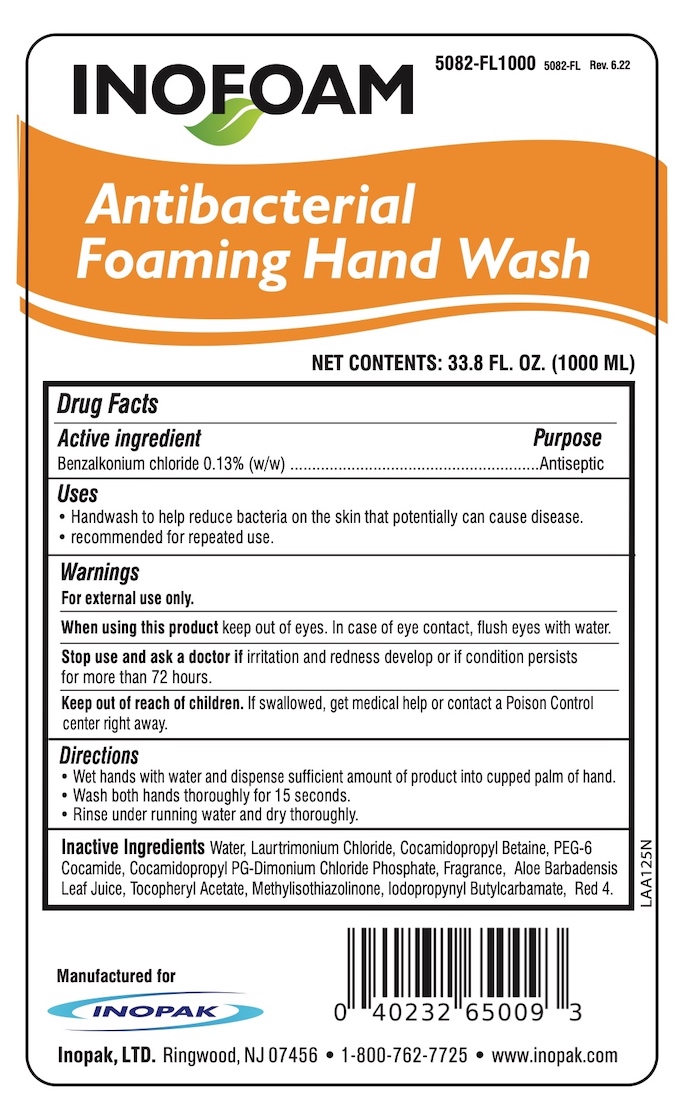 DRUG LABEL: INOFOAM Antibacterial
NDC: 58575-526 | Form: LIQUID
Manufacturer: Inopak, Ltd
Category: otc | Type: HUMAN OTC DRUG LABEL
Date: 20220629

ACTIVE INGREDIENTS: BENZALKONIUM CHLORIDE 0.13 g/100 mL
INACTIVE INGREDIENTS: IODOPROPYNYL BUTYLCARBAMATE; METHYLISOTHIAZOLINONE; COCAMIDOPROPYL PG-DIMONIUM CHLORIDE PHOSPHATE; COCAMIDOPROPYL BETAINE; PEG-6 COCAMIDE; FD&C RED NO. 4; ALOE VERA LEAF; .ALPHA.-TOCOPHEROL ACETATE; LAURTRIMONIUM CHLORIDE; WATER

INOFOAM Antibacterial Foaming Hand Wash (BZK formula)

Drug Facts

Active ingredient

Benzalkonium chloride 0.13% (w/w)

Purpose

Antiseptic

Uses

- Handwash to help reduce bacteria on the skin that potentially can cause disease.
- recommended for repeated use.

Warnings

For external use only.

When using this product keep out of eyes. In case of eye contact, flush eyes with water.

Stop use and ask a doctor if irritation and redness develop or if condtion persists for more than 72 hours.

Keep out of reach of children. If swallowed, get medical help or contact a Poison Control Center right away.

Directions

- Wet hands with water and dispense sufficient amount of product into cupped palm of hand.
- Wash both hands thoroughly for 15 seconds.
- Rince under running water and dry thoroughly.

INACTIVE INGREDIENT

Inactive ingredients Water, Laurtrimonium Chloride, Cocamidopropyl Betaine, PEG-6 Cocamide, Cocamidopropyl PG-Dimonium Chloride Phosphate, Fragrance, Aloe Barbadensis Leaf Juice, Tocopheryl Acetate, Methylisothiazolinone, Iodopropyl Butylcarbamate, Red 4.

Manufactured forr Inopak, LTD., Ringwood, NJ 07456

1-800-767-7725 • www.inopak.com

PACKAGE LABEL

INOFOAM

Antibacterial Foaming Hand Wash

NET CONTENTS: 33.8 FL. OZ. (1000 ML)